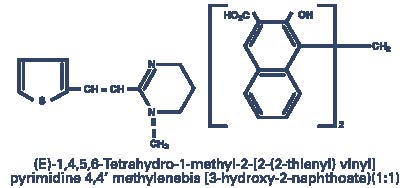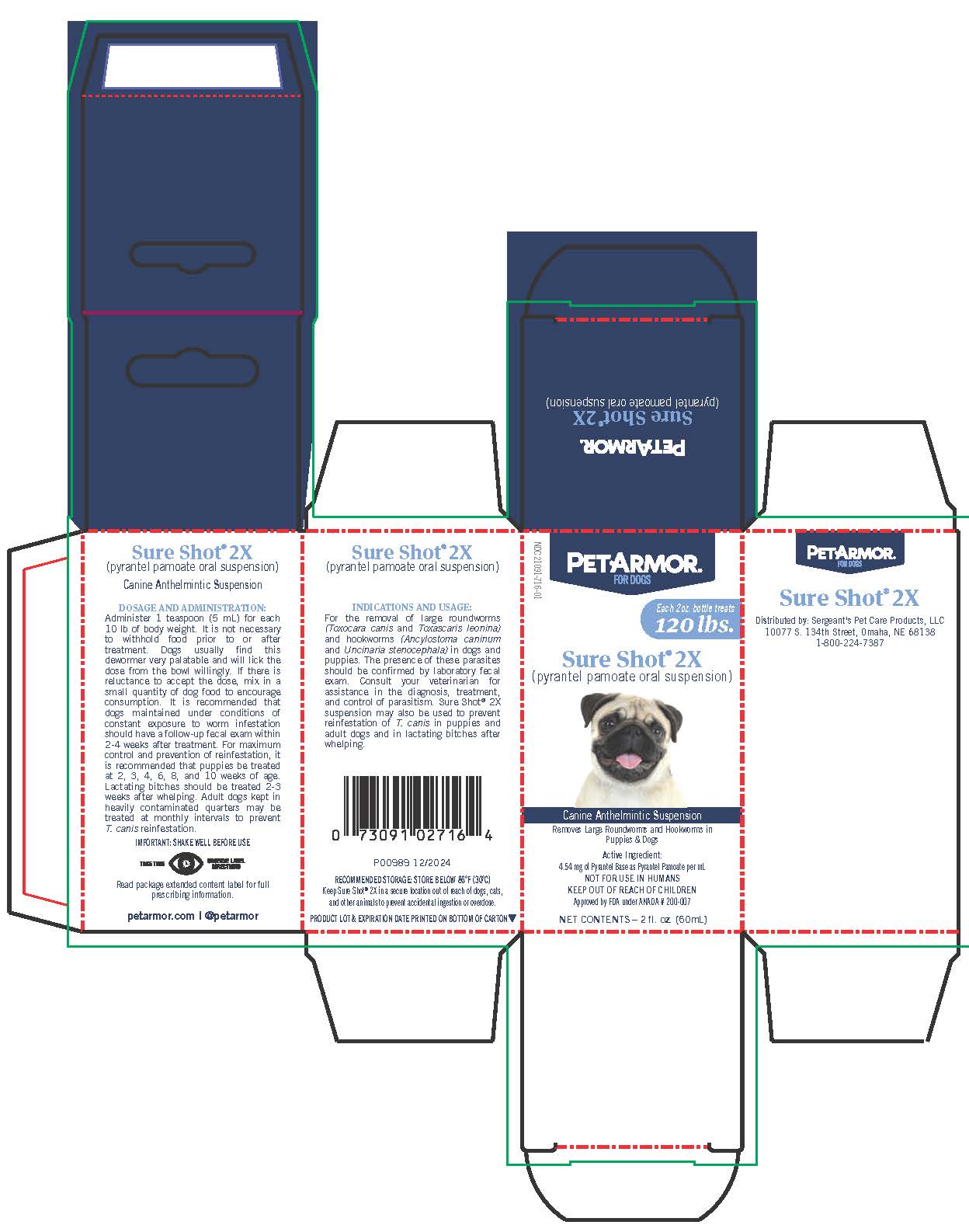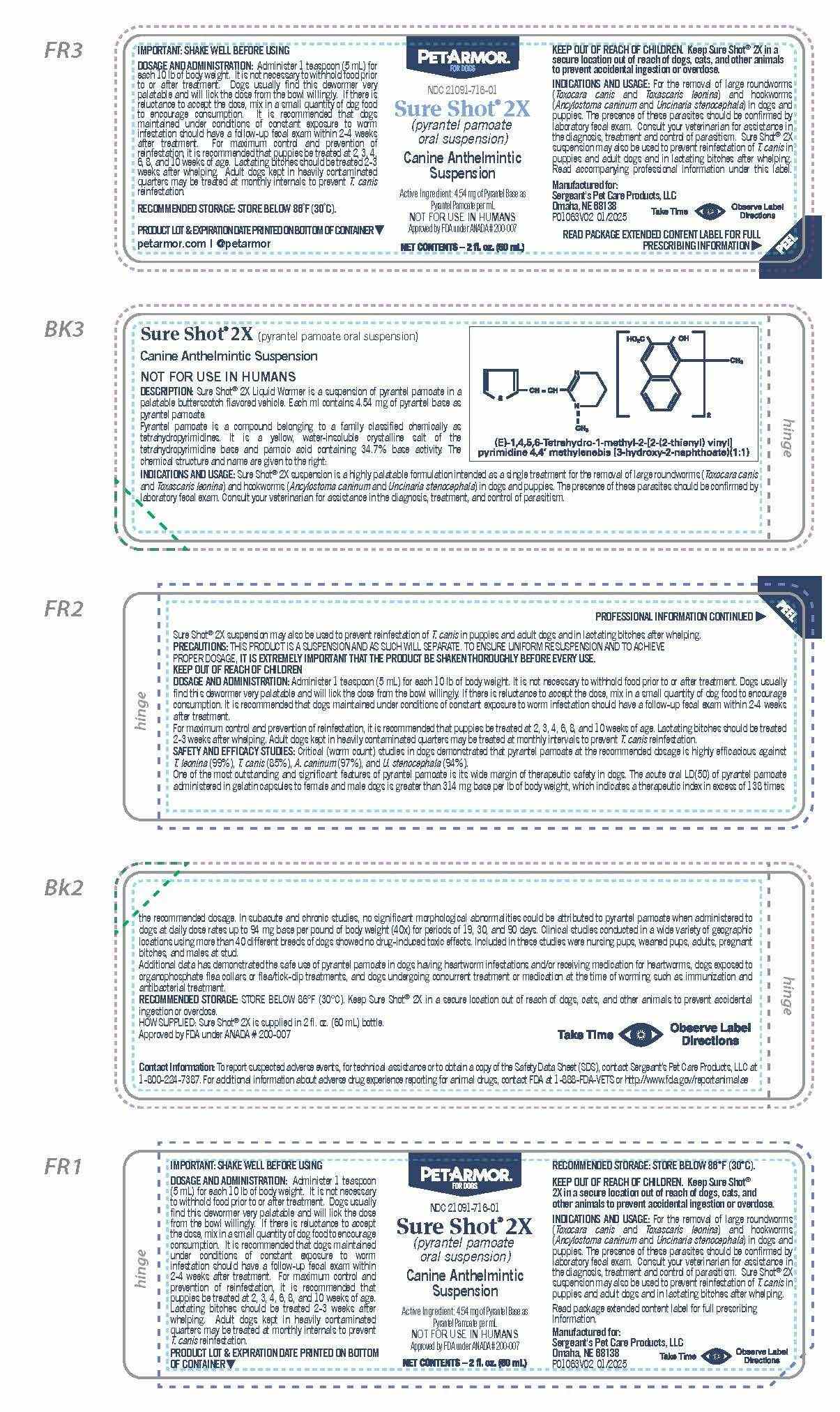 DRUG LABEL: PetArmor Sure Shot 2X
NDC: 21091-716 | Form: LIQUID
Manufacturer: Sergeant's Pet Care Products, LLC
Category: animal | Type: OTC ANIMAL DRUG LABEL
Date: 20250807

ACTIVE INGREDIENTS: PYRANTEL PAMOATE 4.54 mg/1 mL
INACTIVE INGREDIENTS: Methylparaben Sodium

PETARMOR®
FOR DOGS
Sure Shot® 2X
(pyrantel pamoate)

Extended Content Label Panel FR3

IMPORTANT: SHAKE WELL BEFORE USING
DOSAGE AND ADMINISTRATION: Administer 1 teaspoon (5 mL) for each 10 lb of body weight. It is not necessary to withhold food prior to or after treatment. Dogs usually find this dewormer very palatable and will lick the dose from the bowl willingly. If there is reluctance to accept the dose, mix in a small quantity of dog food to encourage consumption. It is recommended that dogs maintained under conditions of constant exposure to worm infestation should have a follow-up fecal exam within 2-4 weeks after treatment. For maximum control and prevention of reinfestation, it is recommended that puppies be treated at 2, 3, 4, 6, 8, and 10 weeks of age. Lactating bitches should be treated 2-3 weeks after whelping. Adult dogs kept in heavily contaminated quarters may be treated at monthly internals to prevent T. canis reinfestation.

RECOMMENDED STORAGE: STORE BELOW 86˚F (30˚C).

PRODUCT LOT & EXPIRATION DATE PRINTED ON BOTTOM OF CONTAINER

petarmor.com | @petarmor

PETARMOR FOR DOGS

NDC 21091-716-01

Sure Shot® 2X

(pyrantel pamoate oral suspension)

Canine Anthelmintic Suspension

Active Ingredient: 4.54 mg of Pyrantel Base as

Pyrantel Pamoate per mL

NOT FOR USE IN HUMANS

Approved by FDA under ANADA # 200-007

NET CONTENTS – 2 fl. oz. (60 mL)

KEEP OUT OF REACH OF CHILDREN. Keep Sure Shot® 2X in a secure location out of reach of dogs, cats, and other animals to prevent accidental ingestion or overdose.

INDICATIONS AND USAGE: For the removal of large roundworms (Toxocara canis and Toxascaris leonina) and hookworms (Ancylostoma caninum and Uncinaria stenocephala) in dogs and puppies. The presence of these parasites should be confirmed by laboratory fecal exam. Consult your veterinarian for assistance in the diagnosis, treatment and control of parasitism. Sure Shot® 2X suspension may also be used to prevent reinfestation of T. canis in puppies and adult dogs and in lactating bitches after whelping.

Read accompanying professional information under this label.

Manufactured for:

Sergeant's Pet Care Products, LLC
Omaha, NE 68138

P01063V02 01/2025

Take Time (Eye Symbol) Observe Label Directions

READ PACKAGE EXTENDED CONTENT LABEL FOR FULL PRESCRIBING INFORMATION

(PEEL)

Extended Content Label Panel BK3

Sure Shot® 2X (pyrantel pamoate oral suspension)

Canine Anthelmintic Suspension

NOT FOR USE IN HUMANS

DESCRIPTION: Sure Shot® 2X Liquid Wormer is a suspension of pyrantel pamoate in a palatable butterscotch flavored vehicle. Each mL contains 4.54 mg of pyrantel base as pyrantel pamoate.

Pyrantel pamoate is a compound belonging to a family classified chemically as tetrahydropyrimidines. It is a yellow, water-insoluble crystalline salt of the tetrahydropyrimidine base and pamoic acid containing 34.7% base activity. The chemical structure and name are given to the right:

INDICATIONS AND USAGE: Sure Shot® 2X suspension is a highly palatable formulation intended as a single treatment for the removal of large roundworms (Toxocara canis and Toxascaris leonina) and hookworms (Ancylostoma caninum and Uncinaria stenocephala) in dogs and puppies. The presence of these parasites should be confirmed by laboratory fecal exam. Consult your veterinarian for assistance in the diagnosis, treatment, and control of parasitism.

Extended Content Label Panel FR2

Sure Shot® 2X suspension may also be used to prevent reinfestation of T. canis in puppies and adult dogs and in lactating bitches after whelping.

PRECAUTIONS: THIS PRODUCT IS A SUSPENSION AND AS SUCH WILL SEPARATE. TO ENSURE UNIFORM RESUSPENSION AND TO ACHIEVE
PROPER DOSAGE, IT IS EXTREMELY IMPORTANT THAT THE PRODUCT BE SHAKEN THOROUGHLY BEFORE EVERY USE.

KEEP OUT OF REACH OF CHILDREN

DOSAGE AND ADMINISTRATION: Administer 1 teaspoon (5 mL) for each 10 lb of bodyweight. It is not necessary to withhold food prior to or after treatment. Dogs usually find this dewormer very palatable and will lick the dose from the bowl willingly. If there is reluctance to accept the dose, mix in a small quantity of dog food to encourage consumption. It is recommended that dogs maintained under conditions of constant exposure to worm infestation should have a follow-up fecal exam within 2-4 weeks after treatment.

For maximum control and prevention of reinfestation, it is recommended that puppies be treated at 2, 3, 4, 6, 8, and 10 weeks of age. Lactating bitches should be treated 2-3 weeks after whelping. Adult dogs kept in heavily contaminated quarters may be treated at monthly intervals to prevent T. canis reinfestation.

SAFETY AND EFFICACY STUDIES: Critical (worm count) studies in dogs demonstrated that pyrantel pamoate at the recommended dosage is highly efficacious against T. leonina (99%), T. canis (85%), A. caninum (97%), and U. stenocephala (94%).

One of the most outstanding and significant features of pyrantel pamoate is its wide margin of therapeutic safety in dogs. The acute oral LD(50) of pyrantel pamoate administered in gelatin capsules to female and male dogs is greater than 314 mg base per lb of body weight, which indicates a therapeutic index in excess of 138 times

Extended Content Label Panel BK2

the recommended dosage. In subacute and chronic studies, no significant morphological abnormalities could be attributed to pyrantel pamoate when administered to dogs at daily dose rates up to 94 mg base per pound of body weight (40x) for periods of 19, 30, and 90 days. Clinical studies conducted in a wide variety of geographic locations using more than 40 different breeds of dogs showed no drug-induced toxic effects. Included in these studies were nursing pups, weaned pups, adults, pregnant bitches, and males at stud.

Additional data has demonstrated the safe use of pyrantel pamoate in dogs having heartworm infestations and/or receiving medication for heartworms, dogs exposed to organophosphate flea collars or flea/tick-dip treatments, and dogs undergoing concurrent treatment or medication at the time of worming such as immunization and antibacterial treatment.

RECOMMENDED STORAGE: STORE BELOW 86°F (30°C). Keep Sure Shot® 2X in a secure location out of reach of dogs, cats, and other animals to prevent accidental ingestion or overdose.

HOW SUPPLIED: Sure Shot® 2X is supplied in 2 fl. oz. (60 mL) bottle.

Approved by FDA under ANADA # 200-007

Take Time (Eye Symbol) Observe Label Directions

Contact Information: To report suspected adverse events, for technical assistance or to obtain a copy of the Safety Data Sheet (SDS), contact Sergeant’s Pet Care Products, LLC at 1-800-224-7387. For additional information about adverse drug experience reporting for animal drugs, contact FDA at 1-888-FDA-VETS or http://www.fda.gov/reportanimalae

Extended Content Label Panel FR1 (Bottom Ply)

IMPORTANT: SHAKE WELL BEFORE USING
DOSAGE AND ADMINISTRATION: Administer 1 teaspoon (5 mL) for each 10 lb of body weight. It is not necessary to withhold food prior to or after treatment. Dogs usually find this dewormer very palatable and will lick the dose from the bowl willingly. If there is reluctance to accept the dose, mix in a small quantity of dog food to encourage consumption. It is recommended that dogs maintained under conditions of constant exposure to worm infestation should have a follow-up fecal exam within 2-4 weeks after treatment. For maximum control and prevention of reinfestation, it is recommended that puppies be treated at 2, 3, 4, 6, 8, and 10 weeks of age. Lactating bitches should be treated 2-3 weeks after whelping. Adult dogs kept in heavily contaminated quarters may be treated at monthly internals to prevent T. canis reinfestation.

PRODUCT LOT & EXPIRATION DATE PRINTED ON BOTTOM OF CONTAINER

PETARMOR®

NDC 21091-716-01

Sure Shot® 2X

(pyrantel pamoate oral suspension)

Canine Anthelmintic Suspension

Active Ingredient: 4.54 mg of Pyrantel Base as

Pyrantel Pamoate per mL

NOT FOR USE IN HUMANS

Approved by FDA under ANADA # 200-007

NET CONTENTS – 2 fl. oz. (60 mL)

RECOMMENDED STORAGE: STORE BELOW 86°F (30°C).

KEEP OUT OF REACH OF CHILDREN. Keep Sure Shot® 2X in a secure location out of reach of dogs, cats, and other animals to prevent accidental ingestion or overdose.

INDICATIONS AND USAGE: For the removal of large roundworms (Toxocara canis and Toxascaris leonina) and hookworms (Ancylostoma caninum and Uncinaria stenocephala) in dogs and puppies. The presence of these parasites should be confirmed by laboratory fecal exam. Consult your veterinarian for assistance in the diagnosis, treatment and control of parasitism. Sure Shot® 2X suspension may also be used to prevent reinfestation of T. canis in puppies and adult dogs and in lactating bitches after whelping.

Read package extended content label for full prescribing Information.

Manufactured for:

Sergeant's Pet Care Products, LLC
Omaha, NE 68138

P01063V02 01/2025

Take Time (Eye Symbol) Observe Label Directions